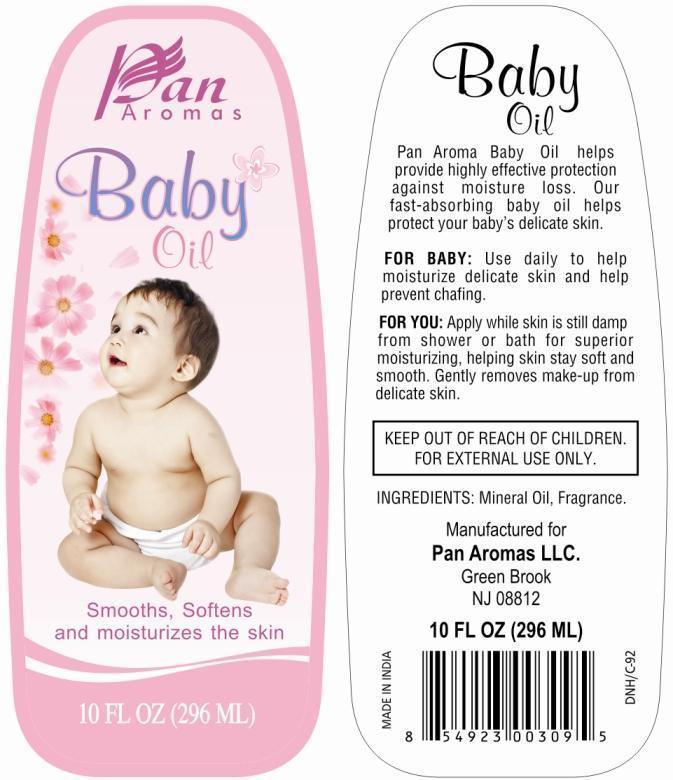 DRUG LABEL: Pan Aromas Baby
NDC: 50346-005 | Form: OIL
Manufacturer: Pan Aromas LLC
Category: otc | Type: HUMAN OTC DRUG LABEL
Date: 20121220

ACTIVE INGREDIENTS: MINERAL OIL 99.9 mL/100 mL

Active Ingredient

Mineral Oil 99.9%

Purpose

Skin Protectant

Uses

- Helps moisturize delicate skin and helps prevent chafing.
- Use after shower or bath for superior moisturizing, helping skin stay soft and smooth.
- Also used as make-up remover from delicate skin.

Warnings

For External Use Only.

Keep out of the reach of children

Children if swallowed get medical help or contact Poison Control Center right away.

Directions

Apply product liberally, as often as necessary.

Inactive Ingredient

Fragrance

PRINCIPAL DISPLAY PANEL

Pan Aromas Baby Oil

NET WT. 10 FL OZ (296 mL)